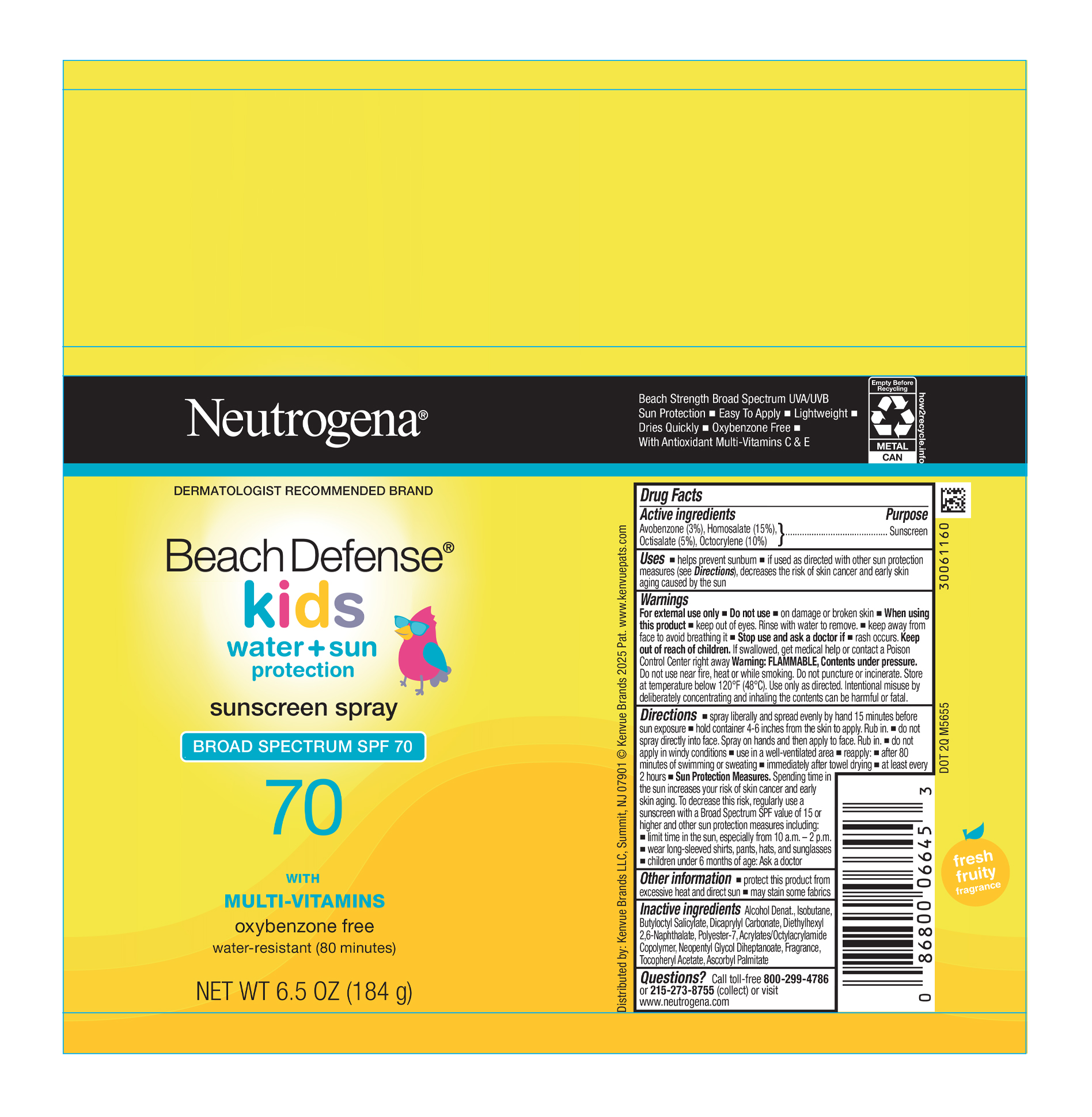 DRUG LABEL: Neutrogena Beach Defense Kids Sunscreen SPF 70
NDC: 69968-0779 | Form: AEROSOL, SPRAY
Manufacturer: Kenvue Brands LLC
Category: otc | Type: HUMAN OTC DRUG LABEL
Date: 20251010

ACTIVE INGREDIENTS: HOMOSALATE 150 mg/1 g; OCTISALATE 50 mg/1 g; OCTOCRYLENE 100 mg/1 g; AVOBENZONE 30 mg/1 g
INACTIVE INGREDIENTS: DIETHYLHEXYL 2,6-NAPHTHALATE; ALPHA-TOCOPHEROL ACETATE; ASCORBYL PALMITATE; ISOBUTANE; BUTYLOCTYL SALICYLATE; DICAPRYLYL CARBONATE; POLYESTER-7; NEOPENTYL GLYCOL DIHEPTANOATE; ALCOHOL; ACRYLATE/ISOBUTYL METHACRYLATE/N-TERT-OCTYLACRYLAMIDE COPOLYMER (75000 MW)

Neutrogena Beach Defense Kids Sunscreen Spray SPF 70

Drug Facts

Active ingredients

Avobenzone 3%, Homosalate 15%, Octisalate 5%, Octocrylene 10%

Purpose

Sunscreen

Uses

- helps prevent sunburn
- if used as directed with other sun protection measures (see Directions), decreases the risk of skin cancer and early skin aging caused by the sun

Warnings

For external use only

Do not use on damaged or broken skin

- When using this product keep out of eyes. Rinse with water to remove.
- keep away from face to avoid breathing it

Stop use and ask a doctor if • rash occurs

Keep out of reach of children. If swallowed, get medical help or contact a Poison Control Center right away

Warning: FLAMMABLE, Contents under pressure. Do not use near fire, heat or while smoking. Do not puncture or incinerate. Store at temperature below 120°F (48°C). Use only as directed. Intentional misuse by deliberately concentrating and inhaling the contents can be harmful or fatal.

Directions

- spray liberally and spread evenly by hand 15 minutes before sun exposure
- hold container 4-6 inches from the skin to apply. Rub in.
- do not spray directly into face. Spray on hands and then apply to face. Rub in.
- do not apply in windy conditions.
- use in a well-ventilated area
- reapply:
- after 80 minutes of swimming or sweating
- immediately after towel drying
- at least every 2 hours
- Sun Protection Measures. Spending time in the sun increases your risk of skin cancer and early skin aging. To decrease this risk, regularly use a sunscreen with a Broad Spectrum SPF value of 15 or higher and other sun protection measures including:
- limit time in the sun, especially from 10 a.m. – 2 p.m.
- wear long-sleeved shirts, pants, hats, and sunglasses
- children under 6 months of age: Ask a doctor

Other information

- protect this product from excessive heat and direct sun
- may stain some fabrics

Inactive ingredients

Alcohol Denat., Isobutane, Butyloctyl Salicylate, Dicaprylyl Carbonate, Diethylhexyl 2,6-Naphthalate, Polyester-7, Acrylates/Octylacrylamide Copolymer, Neopentyl Glycol Diheptanoate, Fragrance, Tocopheryl Acetate, Ascorbyl Palmitate

Questions?

Call toll-free 800-299-4786 or 215-273-8755 (collect) or visit www.neutrogena.com

Distributed by:

Kenvue Brands LLC
Summit, NJ 07901

PRINCIPAL DISPLAY PANEL - 184g Can

Neutrogena®

DERMATOLOGIST RECOMMENDED BRAND

Beach Defense®

kids

water + sun

protection

sunscreen spray

BROAD SPECTRUM SPF 70

70

WITH

MULTI-VITAMINS

oxybenzone free

water - resistant (80 minutes)

NET WT 6.5 OZ (184 g)